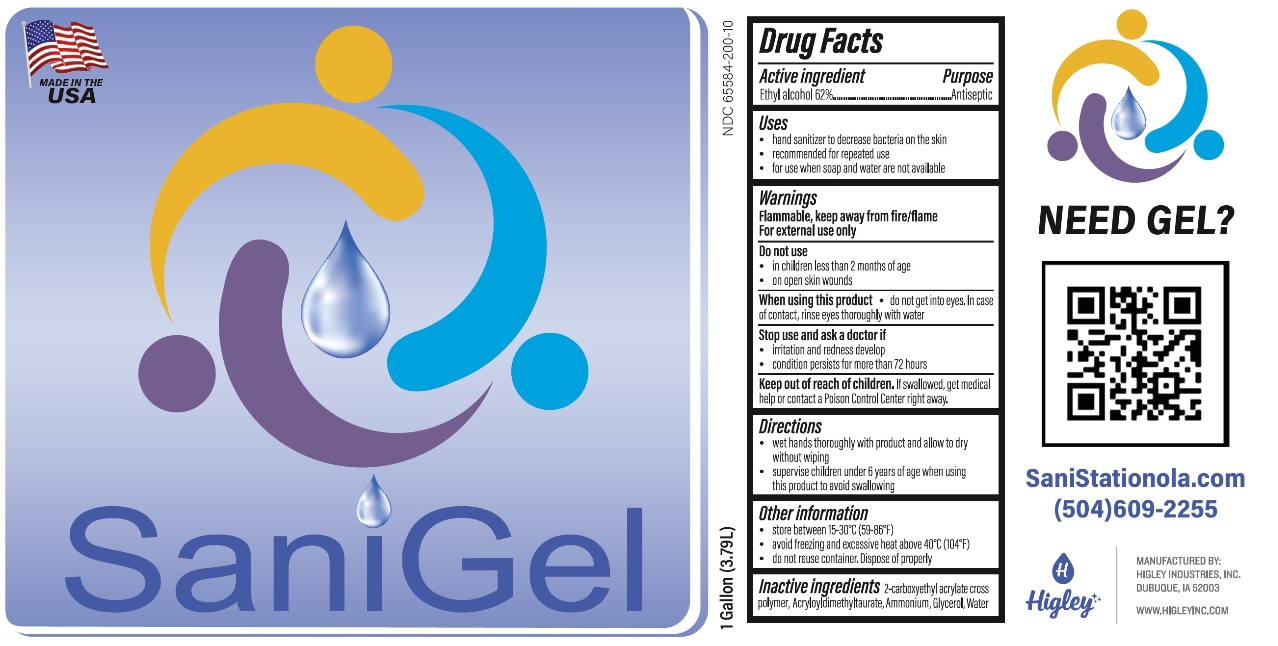 DRUG LABEL: SaniGel
NDC: 65584-200 | Form: GEL
Manufacturer: Higley Industries, Inc.
Category: otc | Type: HUMAN OTC DRUG LABEL
Date: 20200918

ACTIVE INGREDIENTS: ALCOHOL 0.62 mL/1 mL
INACTIVE INGREDIENTS: 2-CARBOXYETHYL ACRYLATE; AMMONIUM ACRYLOYLDIMETHYLTAURATE; GLYCERIN; WATER

SaniGel

Active ingredient

Ethyl alcohol 62%

Purpose

Antiseptic

Uses

• hand sanitizer to decrease bacteria on the skin

• recommended for repeated use

• for use when soap and water are not available.

Warnings

Flammable, keep away from fire/flame

For external use only

Do not use

• in children less than 2 months of age

• on open skin wounds

When using this product • do not get into eyes. In case of contact, rinse eyes thoroughly with water

Stop use and ask a doctor if

• irritation and redness develop

• condition persists for more than 72 hours

Keep out of reach of children. If swallowed, get medical help or contact a Poison Control Center right away.

Directions

• wet hands thoroughly with product and allow to dry without wiping

• supervise children under 6 years of age when using this product to avoid swallowing

Other information

• store between 15-30°C (59-86°F)

• avoid freezing and excessive heat above 40°C (104°F)

• do not reuse container. Dispose of properly

INACTIVE INGREDIENT

Inactive ingredients 2-carboxyethyl acrylate crosspolymer, Acryloyldimethyltaurate, Ammonium, Glycerol, Water

MADE IN THE USA

NEED GEL?

SaniStationola.com

(504) 609-2255

MANUFACTURED BY:

HIGLEY INDUSTRIES, INC.

DUBUQUE, IA 52003

WWW.HIGLEYINC.COM